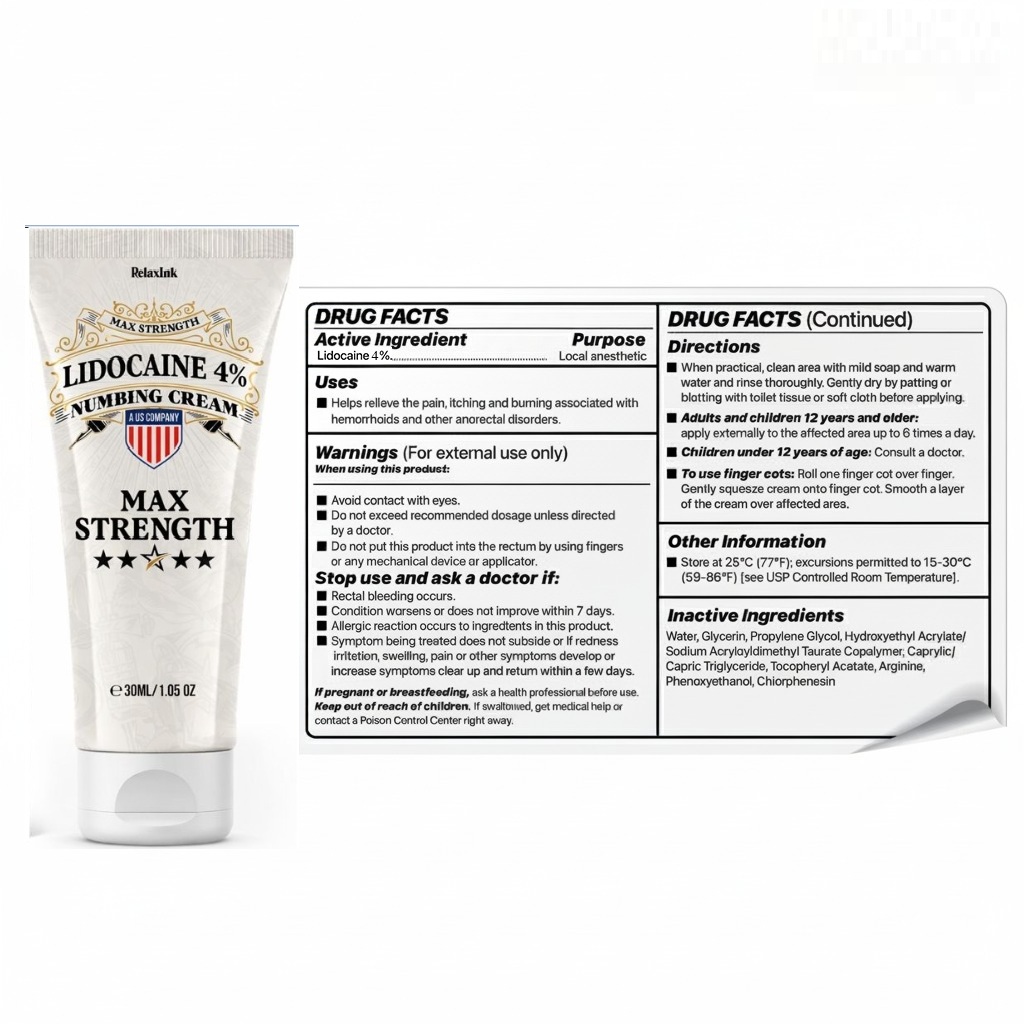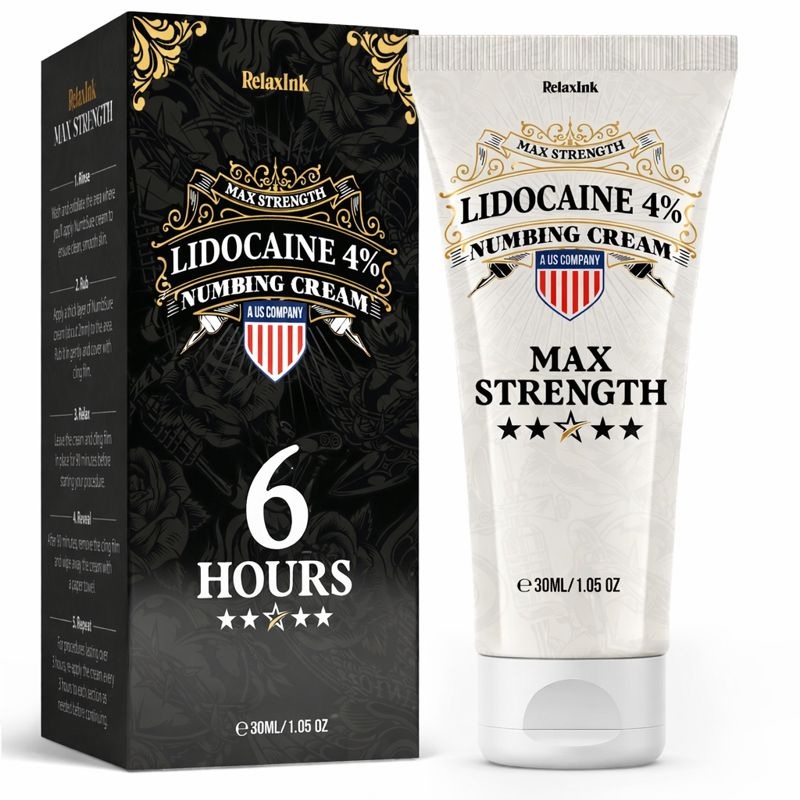 DRUG LABEL: RelaxInk LIDOCAINE
NDC: 83714-0004 | Form: CREAM
Manufacturer: Hambli Limited
Category: otc | Type: HUMAN OTC DRUG LABEL
Date: 20260215

ACTIVE INGREDIENTS: LIDOCAINE 4 g/100 g
INACTIVE INGREDIENTS: CHLORPHENESIN 0.15 g/100 g; GLYCERIN 7 g/100 g; CAPRYLIC/CAPRIC/LAURIC TRIGLYCERIDE 2 g/100 g; PHENOXYETHANOL 0.6 g/100 g; ARGININE 0.7 g/100 g; .ALPHA.-TOCOPHEROL ACETATE, D- 1 g/100 g; WATER 76.35 g/100 g; HYDROXYETHYL ACRYLATE/SODIUM ACRYLOYLDIMETHYL TAURATE COPOLYMER (45000 MPA.S AT 1%) 3.2 g/100 g; PROPYLENE GLYCOL 5 g/100 g

Warnings

(For external use only)
When using this product:

Avoid contact with eyes.
Do not exceed recommended dosage unless directed
by a doctor.
Do not put this product into the rectum by using fingers
or any mechanical device or applicator.
Stop use and ask a doctor if:
Rectal bleeding occurs.
Condition worsens or does not improve within 7 days.
Allergic reaction occurs to ingredients in this product.
Symptom being treated does not subside or if redness
irritation, swelling, pain or other symptoms develop or
increase symptoms clear up and return within a few days.
If pregnant or breastfeeding, ask a health professional before use.
Keep out of reach of children. If swallowed, get medical help or
contact a Poison Control Center right away.

Directions
When practical, clean area with mild soap and warm
water and rinse thoroughly. Gently dry by patting or
blotting with toilet tissue or soft cloth before applying.
Adults and children 12 years and older:
apply externally to the affected area up to 6 times a day.

For the temporary relief of pain and discomfort associated with anorectal disorders.

Keep out of reach of children.

Inactive Ingredients
Water, Glycerin, Propylene Glycol, Hydroxyethyl Acrylate/
Sodium Acryloyldimethyl Taurate Copolymer, Caprylic/
Capric Triglyceride, Tocopheryl Acetate, Arginine,
Phenoxyethanol, Chlorphenesin

Uses
Helps relieve the pain, itching and burning associated with
hemorrhoids and other anorectal disorders.

Avoid contact with eyes.
Do not exceed recommended dosage unless directed
by a doctor.
Do not put this product into the rectum by using fingers
or any mechanical device or applicator.
Stop use and ask a doctor if:
Rectal bleeding occurs.
Condition worsens or does not improve within 7 days.
Allergic reaction occurs to ingredients in this product.
Symptom being treated does not subside or if redness
irritation, swelling, pain or other symptoms develop or
increase symptoms clear up and return within a few days.
If pregnant or breastfeeding, ask a health professional before use.
Keep out of reach of children. If swallowed, get medical help or
contact a Poison Control Center right away.

PURPOSE

Local anesthetic

ACTIVE INGREDIENT

Lidocaine 4%.

No change yet

Pregnancy Section

Consult your doctor before using it

DRUG FACTS

Active Ingredient
Lidocaine 4%.

Uses
Helps relieve the pain, itching and burning associated with
hemorrhoids and other anorectal disorders.

Warnings (For external use only)
When using this product:

Avoid contact with eyes.
Do not exceed recommended dosage unless directed
by a doctor.
Do not put this product into the rectum by using fingers
or any mechanical device or applicator.
Stop use and ask a doctor if:
Rectal bleeding occurs.
Condition worsens or does not improve within 7 days.
Allergic reaction occurs to ingredients in this product.
Symptom being treated does not subside or if redness
irritation, swelling, pain or other symptoms develop or
increase symptoms clear up and return within a few days.
If pregnant or breastfeeding, ask a health professional before use.
Keep out of reach of children. If swallowed, get medical help or
contact a Poison Control Center right away.

Purpose
Local anesthetic

DRUG FACTS (Continued)
Directions
When practical, clean area with mild soap and warm
water and rinse thoroughly. Gently dry by patting or
blotting with toilet tissue or soft cloth before applying.
Adults and children 12 years and older:
apply externally to the affected area up to 6 times a day.
Children under 12 years of age: Consult a doctor.
To use finger cots: Roll one finger cot over finger.
Gently squeeze cream onto finger cot. Smooth a layer
of the cream over affected area.

Other Information
Store at 25°C (77°F); excursions permitted to 15-30C
(59-86°F) [see USP Controlled Room Temperature].

Inactive Ingredients
Water, Glycerin, Propylene Glycol, Hydroxyethyl Acrylate/
Sodium Acryloyldimethyl Taurate Copolymer, Caprylic/
Capric Triglyceride, Tocopheryl Acetate, Arginine,
Phenoxyethanol, Chlorphenesin